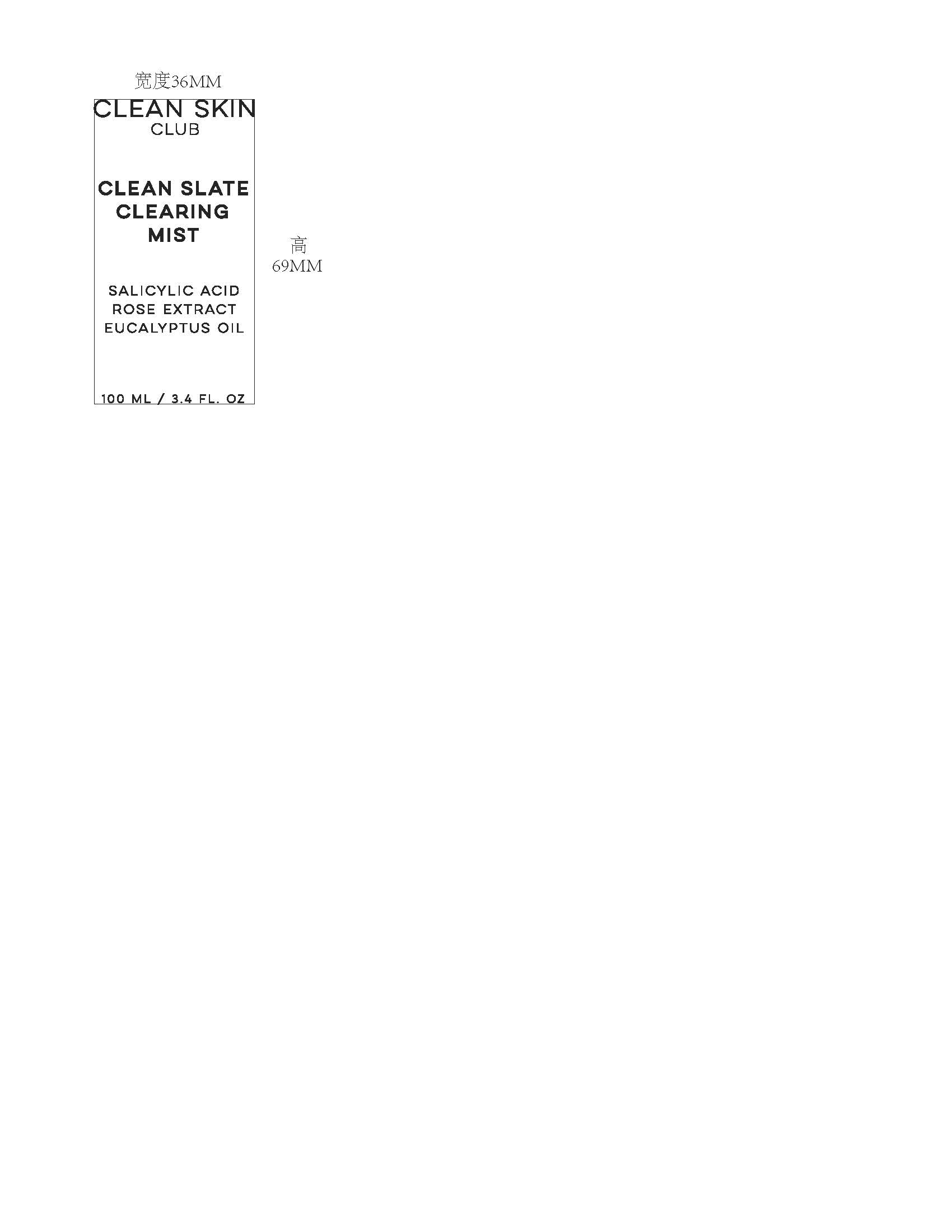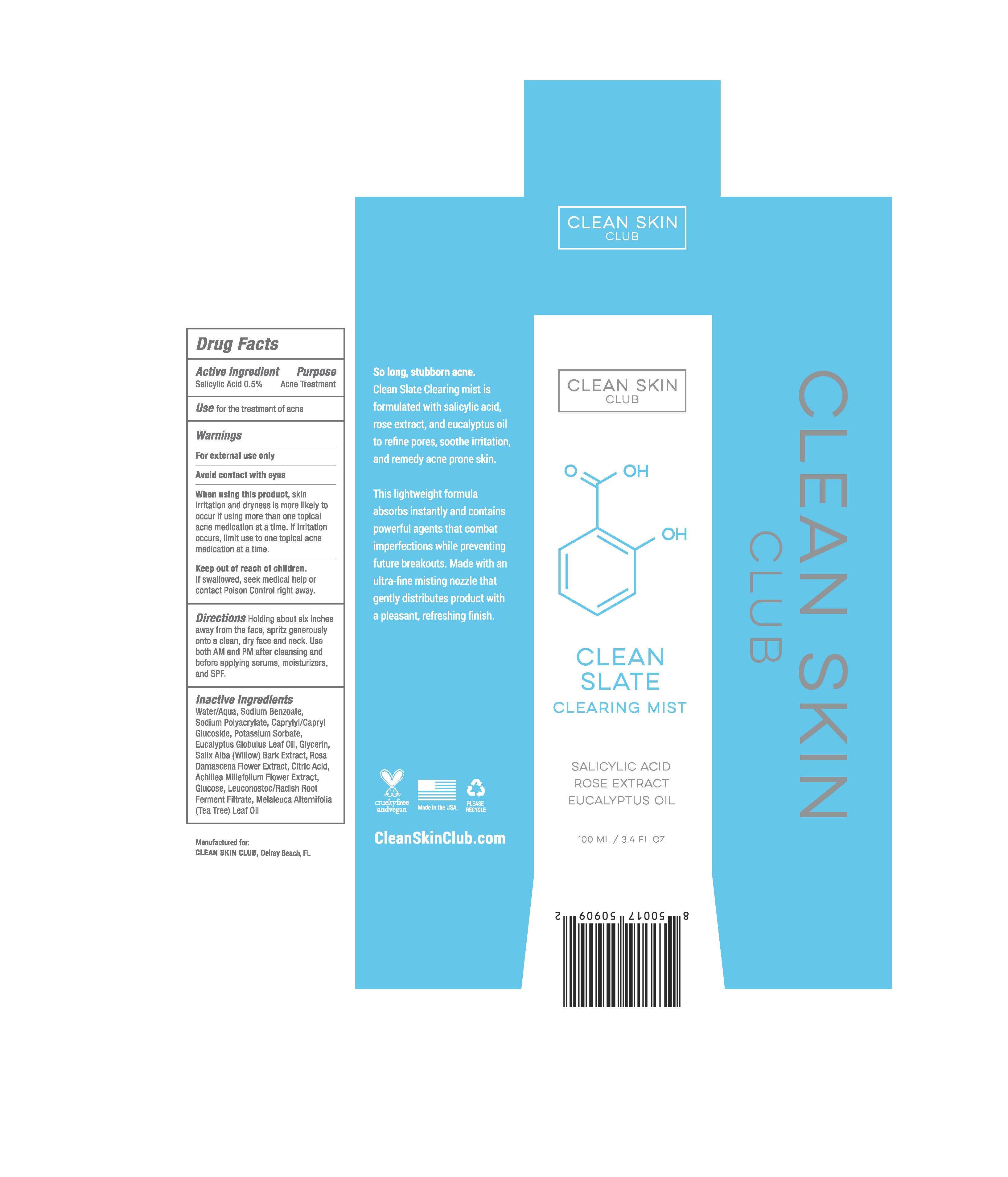 DRUG LABEL: MIST
NDC: 78999-007 | Form: LIQUID
Manufacturer: CLEAN SKIN CLUB
Category: otc | Type: HUMAN OTC DRUG LABEL
Date: 20230210

ACTIVE INGREDIENTS: SALICYLIC ACID 0.5 mg/100 mg
INACTIVE INGREDIENTS: LEUCONOSTOC/RADISH ROOT FERMENT FILTRATE; MELALEUCA ALTERNIFOLIA LEAF; WATER; POTASSIUM SORBATE; EUCALYPTUS GLOBULUS LEAF; GLYCERIN; SALIX ALBA BARK; ROSA DAMASCENA FLOWER; ACHILLEA MILLEFOLIUM FLOWER; SODIUM BENZOATE; SODIUM POLYACRYLATE (8000 MW); CAPRYLYL/CAPRYL OLIGOGLUCOSIDE

CLEAN SKIN CLUB CLEAN SLATE CLEARING MIST

Active Ingredient

Salicylic Acid.... 0.5%

Purpose

Acne Treatment

Use

Use for treatment of acne

Warnings

For external use only

Contact with eyes

Avoid contact with eyes

When using this product, skin irritation and dryness is more likely to occur if using more than one topical acne medication at a time. If irritation occurs, limit use to one topical acne medication at a time.

Keep out of reach of children. If swallowed, seek medical help or contact Poison Control right away.

Directions

Holding about six inches away from the face, spritz generously onto a clean, dry face and neck. Use both AM and PM after cleaning and before applying serums, moisturizers, and SPF.

Inactive Ingredients

Water/Aqua, Sodium Benzoate, Sodium Polyacrylate, Caprylyl/Capryl Glucoside, Potassium Sorbate, Eucalyptus Globulus Leaf Oil, Glycerin, Salix Alba (Willow) Bark Extract, Rosa Damascena Flower Extract, Citric Acid, achillea Milefolium Flower Extract, Glucose, Leuconostoc/Radish Root Ferment Filtrate, Melaleuca Alternifolia (Tea Tree) Leaf Oil.

Primary Package

Bottle